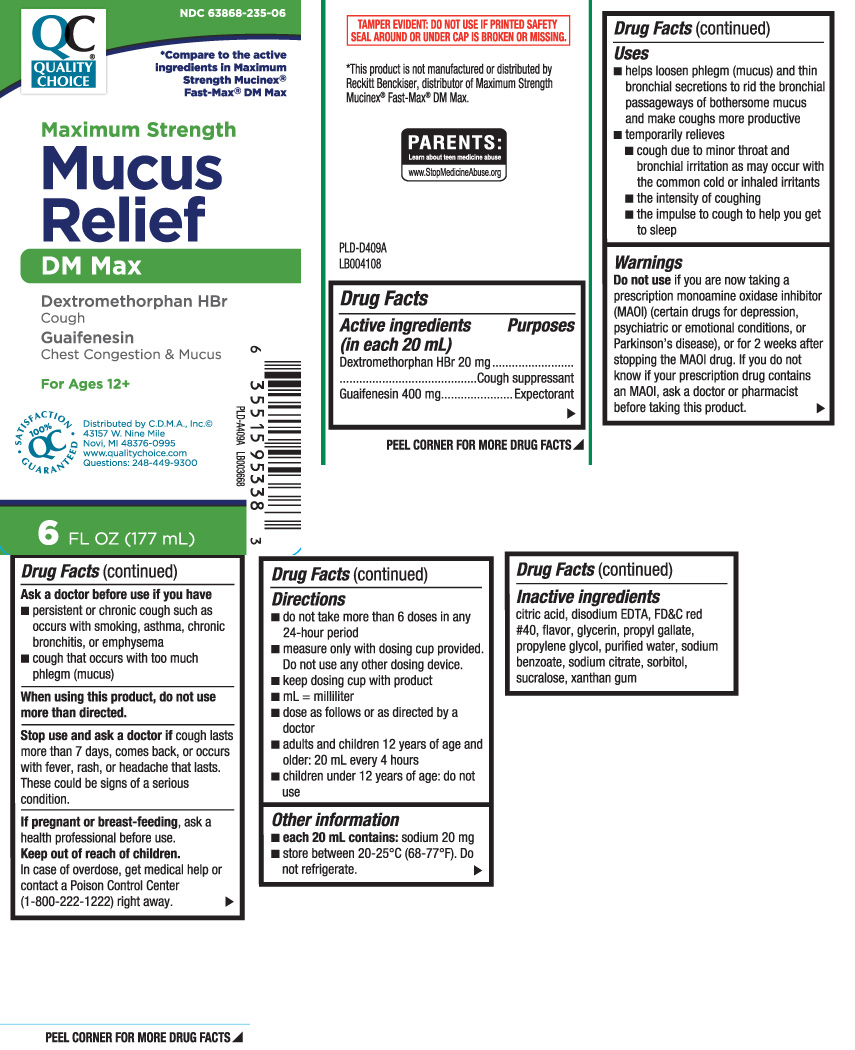 DRUG LABEL: Mucus Relief DM Max
NDC: 63868-235 | Form: LIQUID
Manufacturer: QUALITY CHOICE (Chain Drug Marketing Association)
Category: otc | Type: HUMAN OTC DRUG LABEL
Date: 20240501

ACTIVE INGREDIENTS: DEXTROMETHORPHAN HYDROBROMIDE 20 mg/20 mL; GUAIFENESIN 400 mg/20 mL
INACTIVE INGREDIENTS: ANHYDROUS CITRIC ACID; EDETATE SODIUM; PROPYL GALLATE; SODIUM BENZOATE; SODIUM CITRATE; SORBITOL; FD&C RED NO. 40; GLYCERIN; PROPYLENE GLYCOL; WATER; SUCRALOSE; XANTHAN GUM

Drug Facts

Active ingredients (in each 20 mL)

Dextromethorphan HBr 20 mg

Guaifenesin 400 mg

Purposes

Cough suppressant

Expectorant

Uses

- helps loosen phlegm (mucus) and thin bronchial secretions to rid the bronchial passageways of botherosme mucus and make coughs more productive
- temporarily relieves:
  - cough due to minor throat and bronchial irritation as may occur with the common cold or inhaled irritants
  - the intensity of coughing
  - the impulse to cough to help you get to sleep

Warnings

Do not use

- if you are now taking a prescription monoamine oxidase inhibitor (MAOI) (certain drugs for depression, psychiatric or emotional conditions, or Parkinson's disease), or for 2 weeks after stopping the MAOI drug. If you do not know if your prescription drug contains an MAOI, ask a doctor or pharmacist before taking this product.

Ask a doctor before use if you have

- persistent or chronic cough such as occurs with smoking, asthma, chronic bronchitis or emphysema
- cough that occurs with too much phlegm (mucus)

When using this product,

do not use more than directed

Stop use and ask a doctor if

cough lasts more than 7 days, comes back, or occurs with fever, rash or headache that lasts. These could be signs of a serious condition.

If pregnant or breast-feeding,

ask a health professional before use.

Keep out of reach of children.

In case of overdose, get medical help or contact a Poison Control Center (1-800-222-1222) right away.

Directions

- do not take more than 6 doses in any 24-hour period
- measure only with dosing cup provided. Do not use any other dosing device.
- keep dosing cup with product
- mL = milliliter
- dose as follows or as directed by a doctor
- adults and children 12 years of age and older: 20 mL every 4 hours
- children under 12 years of age: do not use

Other information

- each 20 mL contains: sodium 20 mg
- store between 20-25ºC (68-77ºF). Do not refrigerate

Inactive ingredients

anhydrous citric acid, disodium EDTA, FD&C red #40, flavor, glycerin, propyl gallate, propylene glycol, purified water, sodium benzoate,sodium citrate, sobitol, sucralose, xanthan gum

Principal Display Panel

*Compare to the active ingredients in Maximum Strength Mucinex® Fast-Max® DM Max

Maximum Strength

Mucus Relief DM Max

Dextromethorphan HBr, Cough

Guaifenesin Chest Congestion & Mucus

For Ages 12 +

FL OZ (mL)

*This product is not manufactured or distributed by Reckitt Benckiser, distributor of Maximum Strength Mucinex® Fast-Max® DM Max.

TAMPER EVIDENT: DO NOT USE IF PRINTED SAFETY SEAL AROUND OR UNDER CAP IS BROKEN OR MISSING.

Distributed by C.D.M.A., Inc,©

43157 W. Nine Mile

Novi, MI 48376-0995

www.qualitychoice.com

Question 248-449-9300

Package Label

Quality Choice Maximum Strength Mucus Relief DM Max